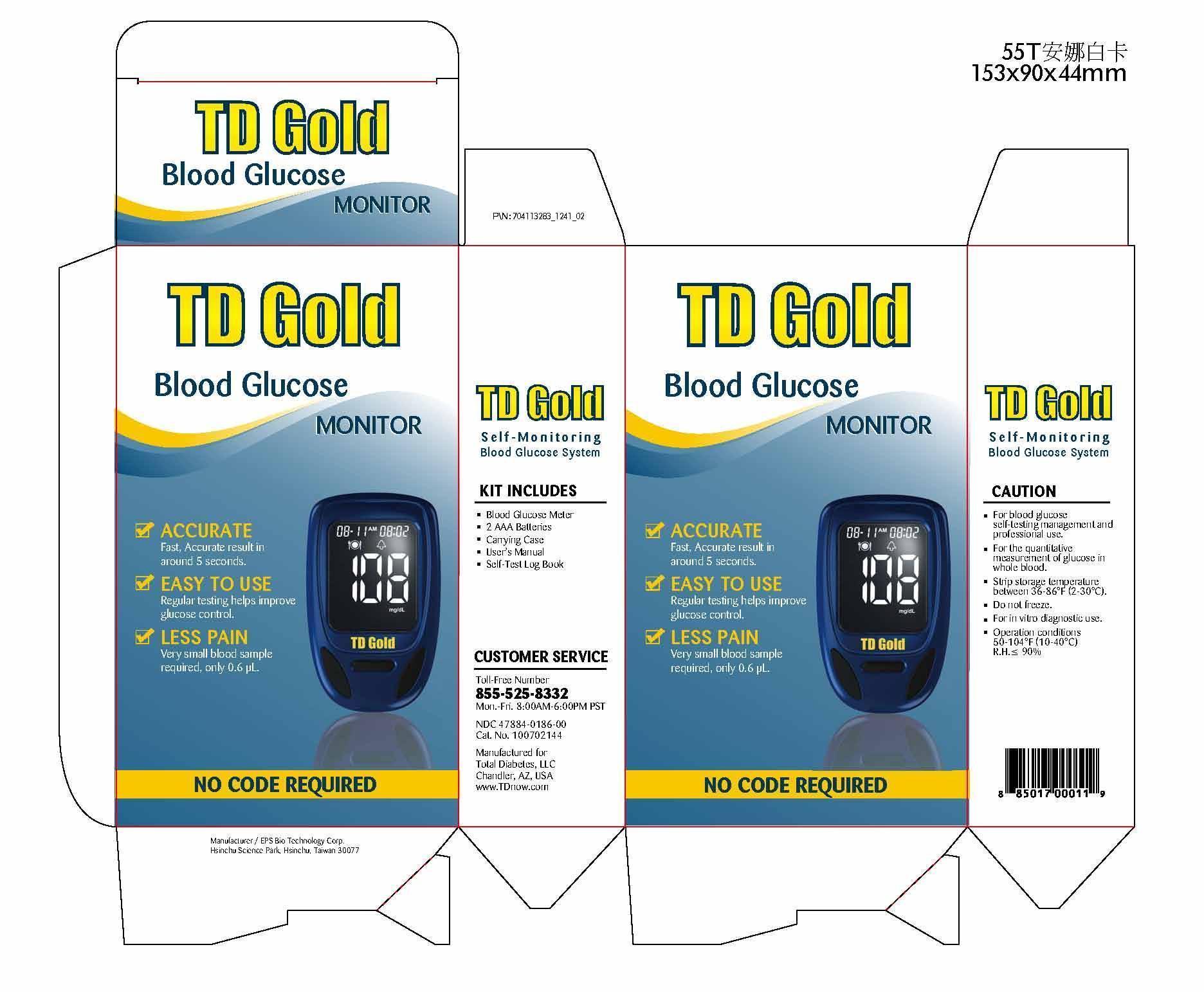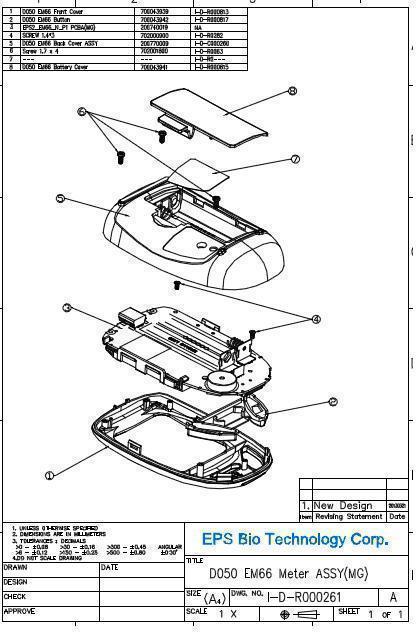 DRUG LABEL: TD Gold Blood Glucose Monitor Set
NDC: 47887-186
Manufacturer: EPS Bio Technology Corp.
Category: other | Type: MEDICAL DEVICE
Date: 20131022

Home Use Medical Device - TD Gold Self-monitoing Blood Glucose System